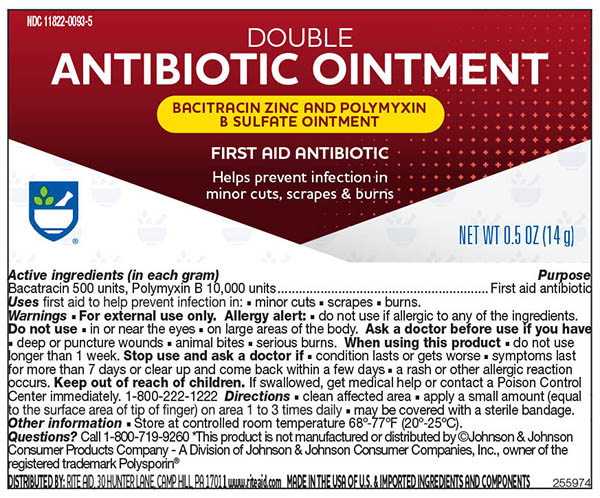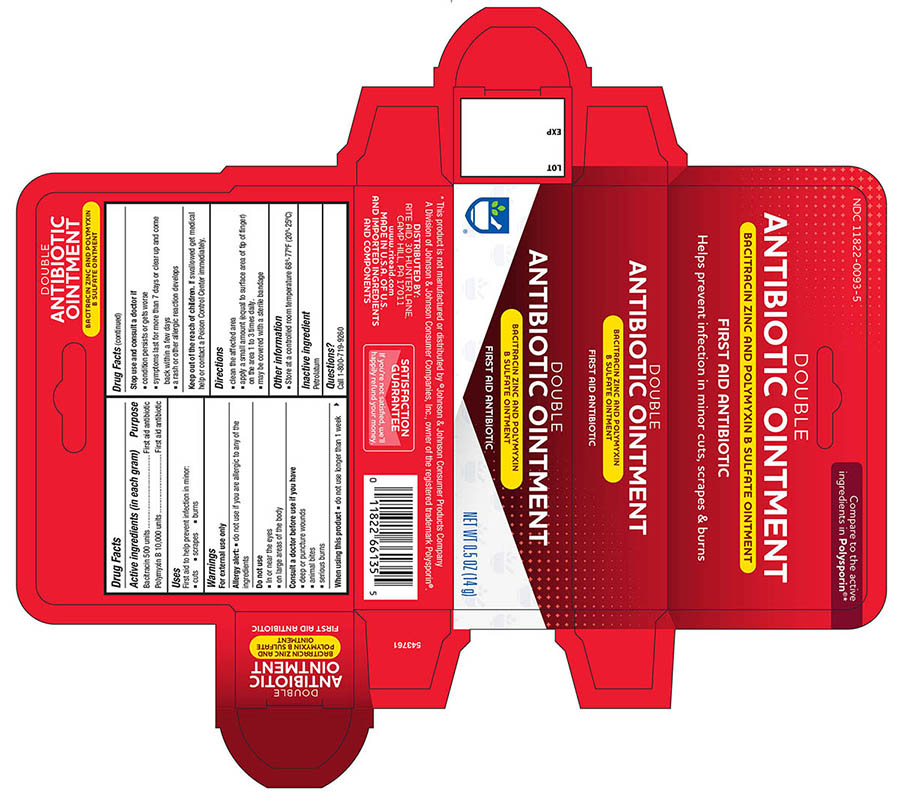 DRUG LABEL: RITE AID Double Antibiotic
NDC: 11822-0093 | Form: OINTMENT
Manufacturer: RITE AID
Category: otc | Type: HUMAN OTC DRUG LABEL
Date: 20241121

ACTIVE INGREDIENTS: BACITRACIN ZINC 500 [USP'U]/1 g; POLYMYXIN B SULFATE 10000 [USP'U]/1 g
INACTIVE INGREDIENTS: PETROLATUM

Active ingredients (In each gram)

Bacitracin 500 units

Polymyxin B Sulfate 10,000 units

Purpose

First aid antibiotic

Uses

First aid to help prevent infection in minor:

- cuts
- scrapes
- burns

Warnings

For external use only

Allergy alert:

- do not use if you are allergic to any of the ingredients

Do not use

- in or near the eyes
- on large areas of the body

Consult a doctor before use if you have

deep or puncture wounds
animal bites
serious burns

When using this product

- do not use longer than 1 week

Keep out of the reach of children.

If swallowed get medical help or contact a Poison Control Center immediately.

Directions

- clean the affected area
- apply a small amount (equal to surface area of tip of finger) on the area 1 to 3 times daily.
- may be covered with a sterile bandage

Inactive ingredient

Petrolatum

Principal display panel -Tube

Double Antibiotic Ointment NDC 11822-0093-5

Bacitracin Zinc - 500 Bacitracin units

Polymixin B Sulfate - 10,000 units

First Aid Antibiotic

NET WT 0.5oz (14g)

Principal Display Panel -Carton

Double Antibiotic Ointment NDC 11822-0093-5

Bacitracin Zinc - 500 Bacitracin units

Polymixin B Sulfate - 10,000 units

First Aid Antibiotic

NET WT 0.5oz (14g)